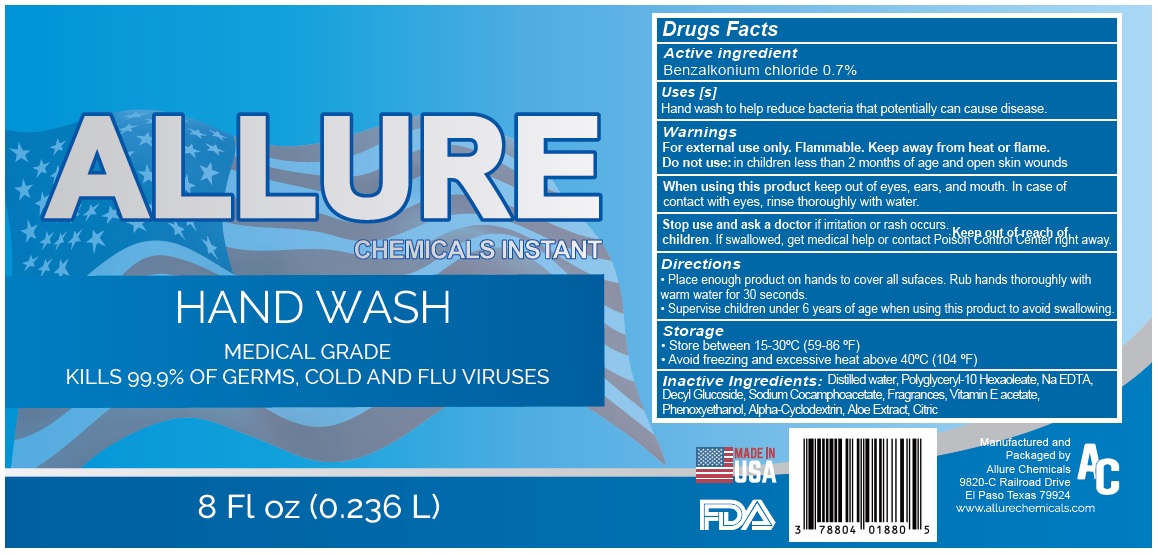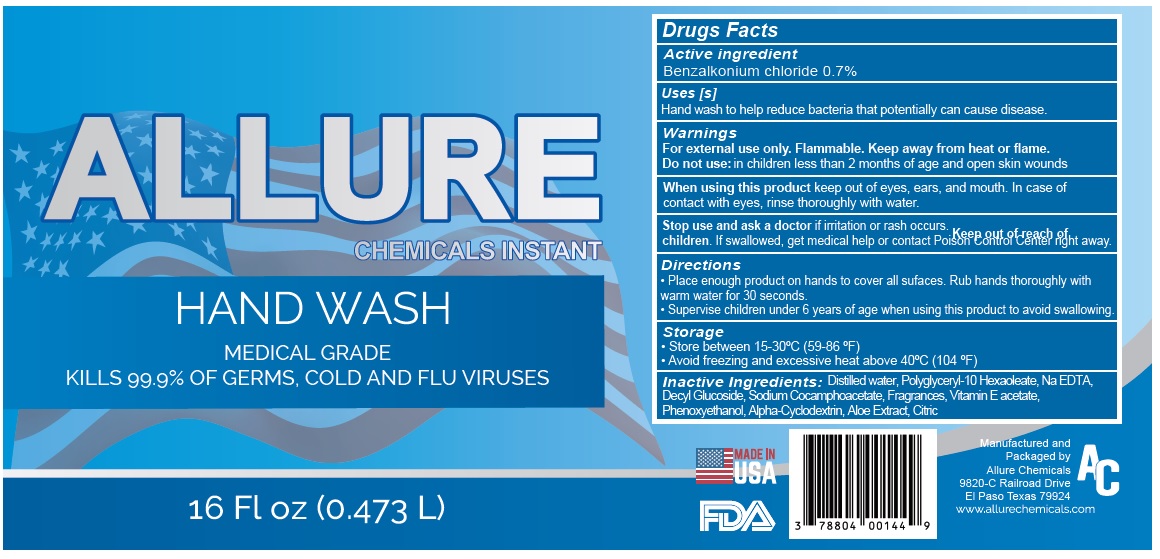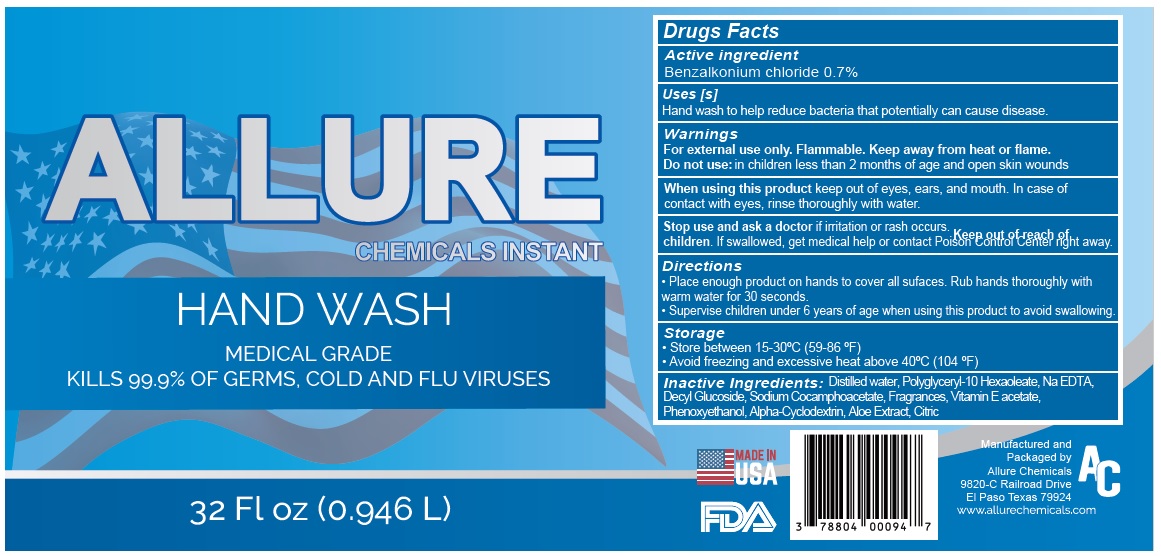 DRUG LABEL: Allure Hand Wash
NDC: 78804-898 | Form: LIQUID
Manufacturer: Allure Chemicals LP
Category: otc | Type: HUMAN OTC DRUG LABEL
Date: 20210506

ACTIVE INGREDIENTS: BENZALKONIUM CHLORIDE 7 g/1 L
INACTIVE INGREDIENTS: WATER; POLYGLYCERYL-10 HEXAOLEATE; EDETATE SODIUM; DECYL GLUCOSIDE; SODIUM COCOAMPHOACETATE; .ALPHA.-TOCOPHEROL ACETATE; PHENOXYETHANOL; ALFADEX; ALOE; CITRIC ACID MONOHYDRATE

ALLURE CHEMICALS INSTANT HAND WASH

Active ingredient

Benzalkonium chloride 0.7%

Purpose

Antibacterial

Uses [s]

Hand wash to help reduce bacteria that potentially can cause disease.

Warnings

For external use only. Flammable. Keep away from heat or flame.

Do not use: in children less than 2 months of age and open skin wounds

When using this product keep out of eyes, ears, and mouth. In case of contact with eyes, rinse thoroughly with water.

Stop use and ask doctor if irritation or rash occurs.

Keep out of reach of children. If swallowed, get medical help or contact Poison Control Center right away.

Directions

• Place enough product on hands to cover all surfaces. Rub hands thoroughly with warm water for 30 seconds.

• Supervise children under 6 years of age when using this product to avoid swallowing.

Storage

• Store between 15-30°C (59-86 °F)

• Avoid freezing and excessive heat above 40°C (104 °F)

Inactive Ingredients:

Distilled water, Polyglyceryl-10 Hexaoleate, Na EDTA, Decyl Glucoside, Sodium Cocoamphoacetate, Fragrances, Vitamin E acetate, Phenoxyethanol, Alpha-Cyclodextrin, Aloe Extract, Citric

ALLURE CHEMICALS INSTANT HAND WASH

MEDICAL GRADE

KILLS 99.9% OF GERMS, COLD AND FLU VIRUSES

Manufactured and Packaged by
Allure Chemicals
9820-C Railroad Drive
El Paso Texas 79924
www.allurechemicals.com

MADE IN USA